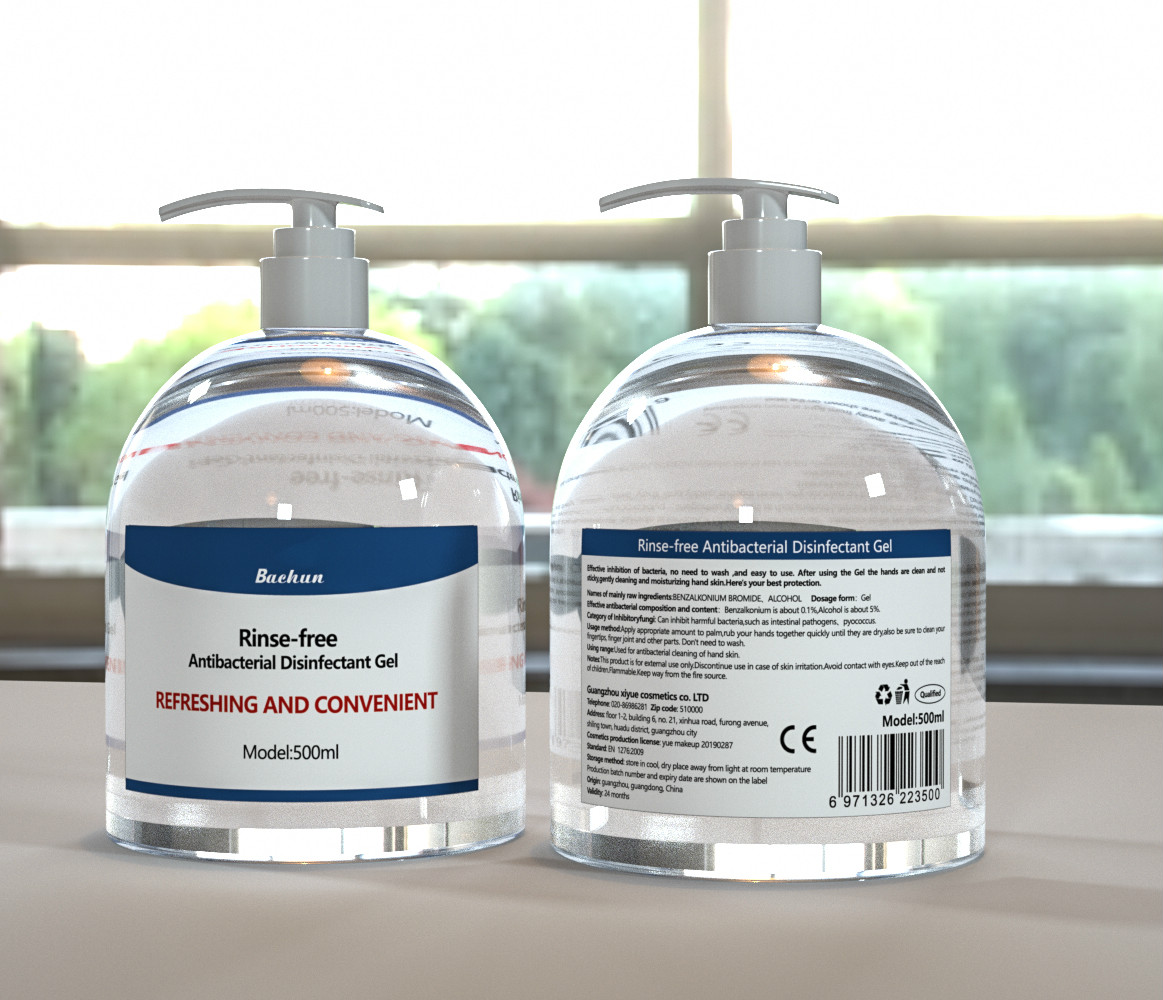 DRUG LABEL: antibacterial rinse free gel
NDC: 78860-001 | Form: GEL
Manufacturer: Guangzhou Xiyue Cosmetics Co.,Ltd
Category: otc | Type: HUMAN OTC DRUG LABEL
Date: 20200609

ACTIVE INGREDIENTS: ALCOHOL 5 mL/100 mL
INACTIVE INGREDIENTS: BENZALKONIUM; BROMIDE ION; WATER

antibacterial rinse-free gel

Active Ingredient(s)

Alcohol 5%

Purpose

Antiseptic, Hand Sanitizer

Use

Can inhibit harmful baterial，such as intestinal pathogens,pyococous

Warnings

this product is fir enternal use only. flammbale.keep away from the fire source

discontinue use in case of skin irritation

WHEN USING

avoid contact with eyes ,keep out of the reach of children

Stop use and ask a doctor if irritation or rash occurs. These may be signs of a serious condition.

Keep out of reach of children.

Directions

apply appropriate amount to palm,rub your hands together quickly until they are dry also be sure to clean your fingerips,finger joint abd cather parts,dont need to wash

Inactive ingredients

BENZALKONIUM, BROMIDE